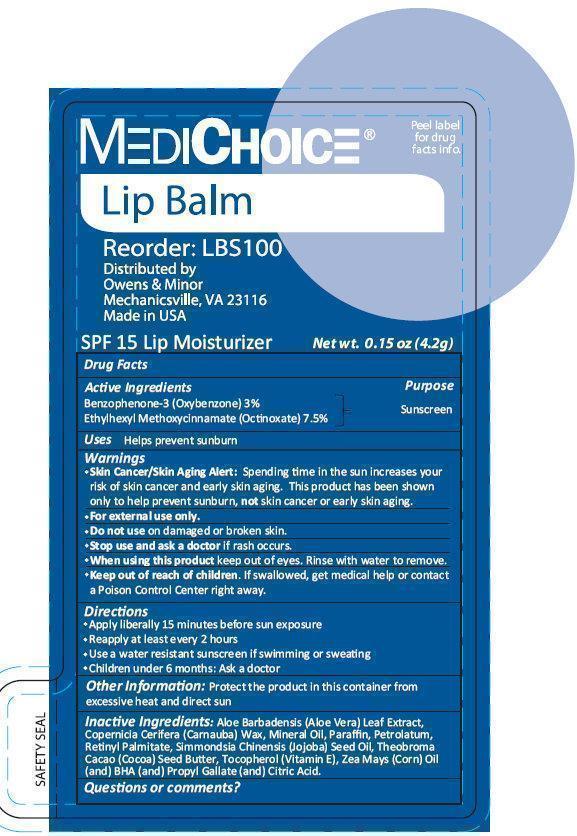 DRUG LABEL: 
                  MediChoice Lip Balm
                
                  

NDC: 39892-0900 | Form: LIPSTICK
Manufacturer: Owens & Minor Inc.
Category: otc | Type: HUMAN OTC DRUG LABEL
Date: 20231209

ACTIVE INGREDIENTS: OXYBENZONE 3 g/100 g; OCTINOXATE 7.5 g/100 g
INACTIVE INGREDIENTS: ALOE VERA LEAF; CARNAUBA WAX; MINERAL OIL; PARAFFIN; PETROLATUM; VITAMIN A PALMITATE; JOJOBA OIL; COCOA BUTTER; TOCOPHEROL; CORN OIL; BUTYLATED HYDROXYANISOLE; PROPYL GALLATE; CITRIC ACID MONOHYDRATE

MediChoice Lip Balm

Active Ingredients

Benzophenone-3 (Oxybenzone) 3%

Ethylhexyl Methoxycinnamate (Octinoxate) 7.5%

Purpose

Sunscreen

Uses

Helps prevent sunburn

Warnings

- Spending time in the sun increases your risk of skin cancer and early skin aging. This product has been shown only to help prevent sunburn, not skin cancer or early skin aging. Skin Cancer / Skin Aging Alert:
- For external use only

Do not use

on damaged or broken skin.

Stop use and ask a doctor

if rash occurs.

When using this product

keep out of eyes. Rinse with water to remove.

Keep out of reach of children.

If swallowed, get medical help or contact a Poison Control Center right away.

Directions

- Apply liberally 15 minutes before sun exposure
- Reapply atleast every 2 hours
- Use a water resistant sunscreen if swimming or sweating
- Children under 6 months: Ask a doctor

Other Information:

Protect the product in this container from excessive heat and direct sun

Inactive Ingredients:

Aloe Barbadensis (Aloe Vera) Leaf Extract, Copernicia Cerifera (Carnauba) Wax, Mineral Oil, Paraffin, Petrolatum, Retinyl Palmitate, Simmondsia Chinensis (Jojoba) Seed Oil, Theobroma Cacao (Cocoa) Seed Butter, Tocopherol (Vitamin E), Zea Mays (Corn) Oil (and) BHA (and) Propyl Gallate (and) Citric Acid.

Product Label

MEDICHOICE Lip Balm SPF 15 Lip Moisturizer Net wt. 0.15 oz (4.2g)